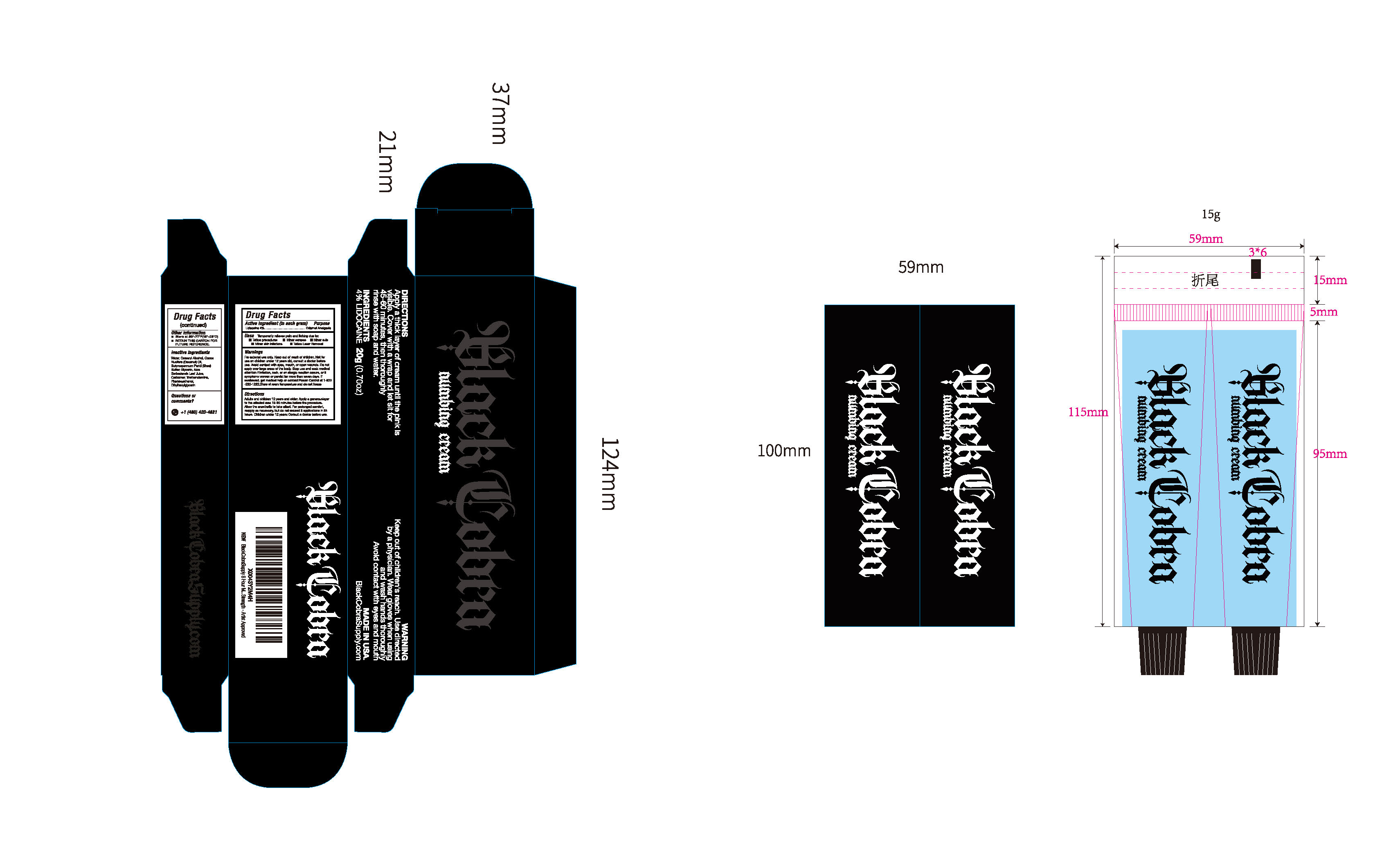 DRUG LABEL: Black Cobra Tattoo Numbing Cream 4% Lidocaine
NDC: 84938-002 | Form: CREAM
Manufacturer: Foshan Sugar Max Cosmetics CO.,Ltd
Category: otc | Type: HUMAN OTC DRUG LABEL
Date: 20260119

ACTIVE INGREDIENTS: LIDOCAINE 0.04 g/1 g
INACTIVE INGREDIENTS: ALOE BARBADENSIS LEAF JUICE; TRIETHANOLAMINE; CETEARYL ALCOHOL; PHENOXYETHANOL; AQUA; ETHYLHEXYLGLYCERIN; COCOS NUCIFERA (COCONUT) OIL; BUTYROSPERMUM PARKII (SHEA) BUTTER; GLYCERIN; CARBOMER

84938-002 Black Cobra Tattoo Numbing Cream 4% Lidocaine

ACTIVE INGREDIENT

Lidocaine 4%

PURPOSE

External Analgesic

INDICATIONS AND USAGE

Temporarily relieves pain and itching due to: Tattoo procedures
Minor scrapes, Minor cuts, Minor skin irritations,
Tattoo Laser Removal

WARNINGS

For external use only.

WHEN USING

Not foruse on children under 12 years old, consult a doctor beforeuse.
Avoid contact with eyes, mouth, or open wounds.

Stop use and seek medicaattention if irritation, rash, or an allergic reaction occurs, or if symptoms worsen or persist for more than seven days.

KEEP OUT OF REACH OF CHILDREN

lf swallowed, get medical help or contact Poison Control at 1-800-222-1222.Store at room temperature and do not freeze

DOSAGE AND ADMINISTRATION

Adults and children 12 years and older: Apply a generouslayerto the affected area 15-30 minutes before the procedure.Allow the anesthetic to take effect. For prolonged comfort,reapply as necessary, but do not exceed 3 applications in 24hours. Children under 12 years: Consult a doctor before use.

INACTIVE INGREDIENT

Aqua
Cetearyl Alcohol
Cocos Nucifera (Coconut) Oil
Butyrospermum Parkii (Shea) Butter
Glycerin
Aloe Barbadensis Leaf Juice
Carbomer
Triethanolamine
Phenoxyethanol
Ethylhexylglycerin